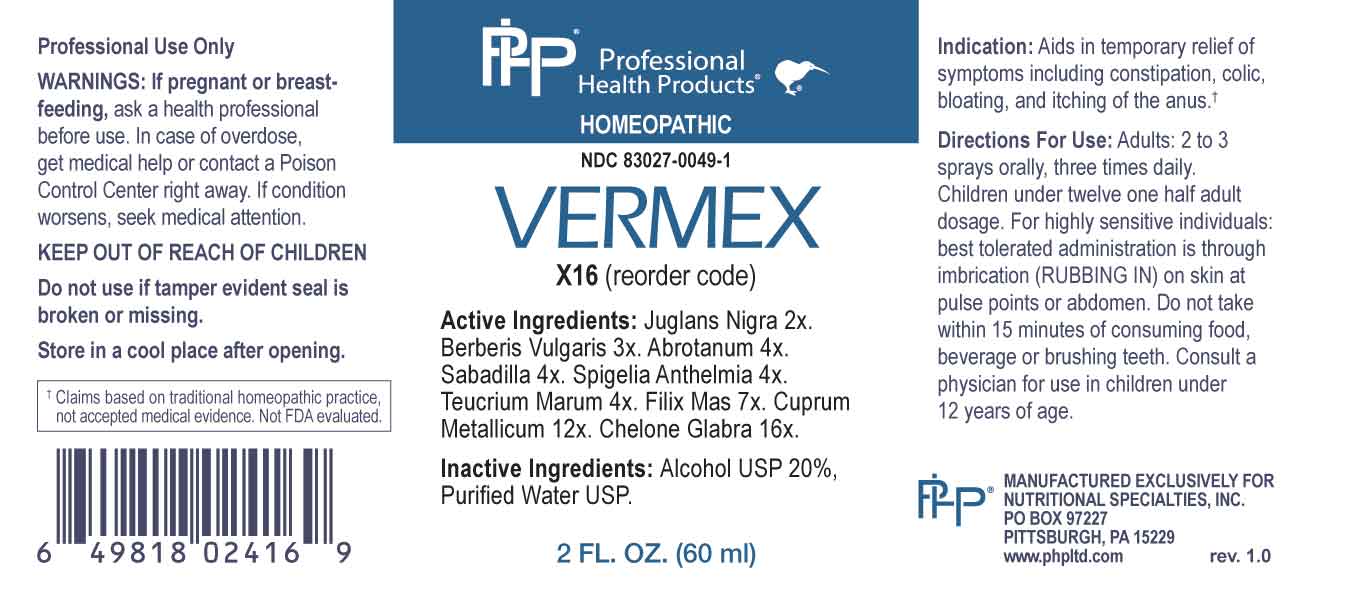 DRUG LABEL: Vermex
NDC: 83027-0049 | Form: SPRAY
Manufacturer: Nutritional Specialties, Inc.
Category: homeopathic | Type: HUMAN OTC DRUG LABEL
Date: 20230724

ACTIVE INGREDIENTS: BLACK WALNUT HUSK 2 [hp_X]/1 mL; BERBERIS VULGARIS ROOT BARK 3 [hp_X]/1 mL; ARTEMISIA ABROTANUM FLOWERING TOP 4 [hp_X]/1 mL; SCHOENOCAULON OFFICINALE SEED 4 [hp_X]/1 mL; SPIGELIA ANTHELMIA WHOLE 4 [hp_X]/1 mL; TEUCRIUM MARUM WHOLE 4 [hp_X]/1 mL; DRYOPTERIS FILIX-MAS ROOT 7 [hp_X]/1 mL; COPPER 12 [hp_X]/1 mL; CHELONE GLABRA WHOLE 16 [hp_X]/1 mL
INACTIVE INGREDIENTS: WATER; ALCOHOL

DRUG FACTS:

ACTIVE INGREDIENTS:

Juglans Nigra 2X, Berberis Vulgaris 3X, Abrotanum 4X, Sabadilla 4X, Spigelia Anthelmia 4X, Teucrium Marum 4X, Filix Mas 7X, Cuprum Metallicum 12X, Chelone Glabra 16X.

PURPOSE:

Aids in temporary relief of symptoms including constipation, colic, bloating, and itching of the anus.†

†Claims based on traditional homeopathic practice, not accepted medical evidence. Not FDA evaluated.

WARNINGS:

Professional Use Only

If pregnant or breast-feeding, ask a health professional before use.

In case of overdose, get medical help or contact a Poison Control Center right away.

If condition worsens, seek medical attention.

KEEP OUT OF REACH OF CHILDREN

Do not use if tamper evident seal is broken or missing.

Store in a cool place after opening

KEEP OUT OF REACH OF CHILDREN:

In case of overdose, get medical help or contact a Poison Control Center right away.

DIRECTIONS:

Adults: 2 to 3 sprays orally, three times daily. Children under twelve one half adult dosage.

For highly sensitive individuals: best tolerated administration is through imbrication (RUBBING IN) on skin at pulse points or abdomen.

Do not take within 15 minutes of consuming food, beverage or brushing teeth. Consult a physician for use in children under 12 years of age.

INDICATIONS:

Aids in temporary relief of symptoms including constipation, colic, bloating, and itching of the anus.†

†Claims based on traditional homeopathic practice, not accepted medical evidence. Not FDA evaluated.

INACTIVE INGREDIENTS:

Alcohol USP 20%, Purified Water USP.

QUESTIONS:

MANUFACTURED EXCLUSIVELY FOR

NUTRITIONAL SPECIALTIES, INC.

PO BOX 97227

PITTSBURG, PA 15229

www.phpltd.com

PACKAGE LABEL DISPLAY:

Professional

Health Products

HOMEOPATHIC

NDC 83027-0049-1

VERMEX

2 FL. OZ (60 ml)